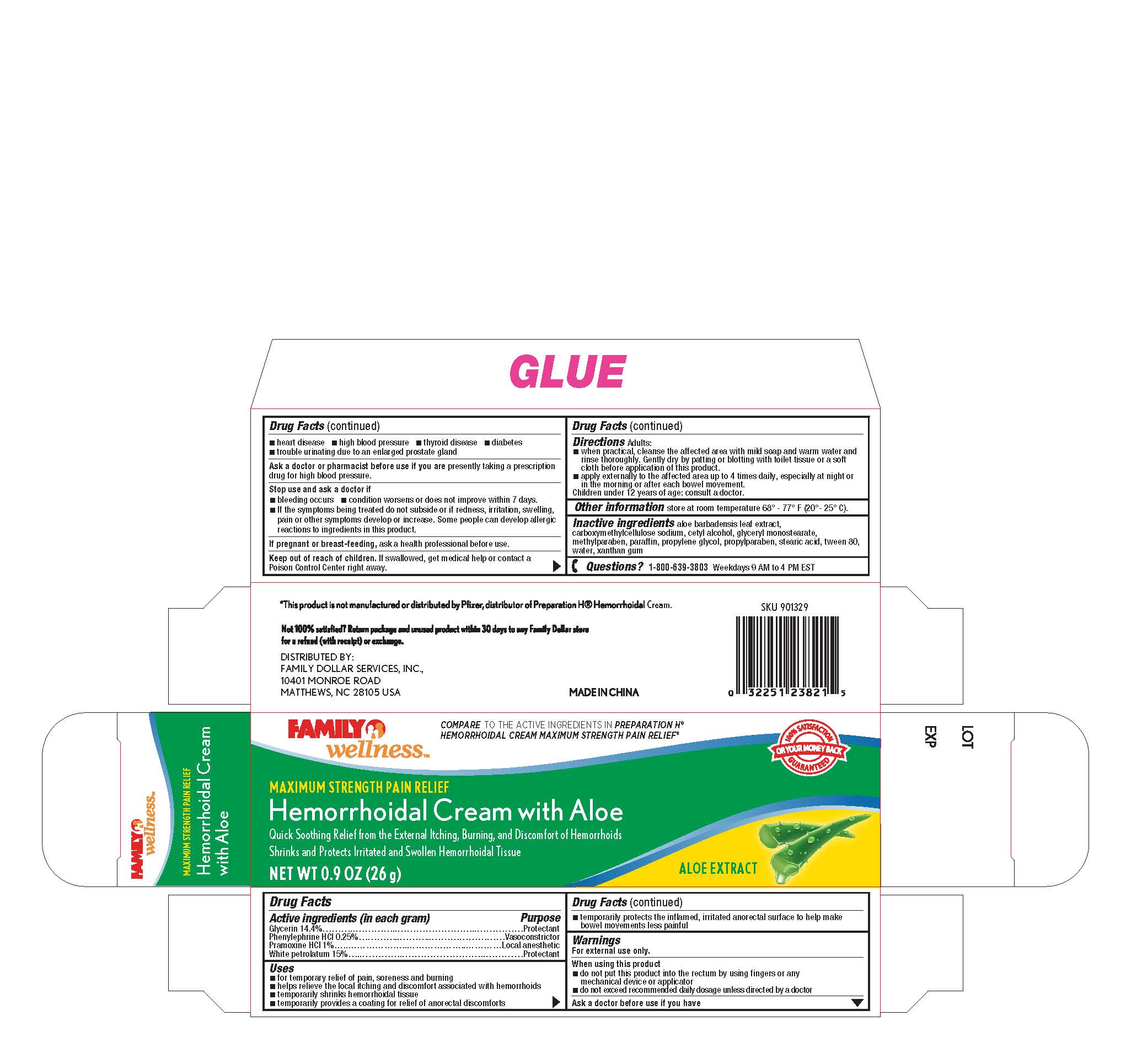 DRUG LABEL: Family Wellness
NDC: 69571-004 | Form: CREAM
Manufacturer: FRONT PHARMACEUTICAL PLC
Category: otc | Type: HUMAN OTC DRUG LABEL
Date: 20231026

ACTIVE INGREDIENTS: GLYCERIN 14.4 g/100 g; PHENYLEPHRINE HYDROCHLORIDE 0.25 g/100 g; PRAMOXINE HYDROCHLORIDE 1 g/100 g; PETROLATUM 15 g/100 g
INACTIVE INGREDIENTS: ALOE VERA LEAF; CARBOXYMETHYLCELLULOSE SODIUM; CETYL ALCOHOL; GLYCERYL MONOSTEARATE; PARAFFIN; METHYLPARABEN; PROPYLENE GLYCOL; PROPYLPARABEN; WATER; XANTHAN GUM; STEARIC ACID; POLYSORBATE 80

Active ingredients (in each gram)

Glycerin 14.4%

Phenylephrine HCL 0.25%

Pramoxine HCL 1%

White petrolatum 15%

Purpose

Protectant

Vasoconstrictor

Local anesthetic

Protectant

Uses

- for temporary relief of pain, soreness and burning
- helps relieve the local itching and discomfort associated with hemorrhoids
- temporarily shrinks hemorrhoidal tissue
- temporarily provides a coating for relief of anorectal discomforts
- temporarily protects the inflamed, irritated anorectal surface to help make bowel movements less painful

Warnings

. For external use only

When using this product

Ask a doctor before use if you have

•heart disease •high blood pressure •thyroid disease •diabetes

•trouble urinating due to an enlarged prostate gland

you are presently taking a prescription Ask a doctor or pharmacist before use if

drug for high blood pressure.

Stop use and ask a doctor if

•bleeding occurs •condition worsens or does not improve within 7 days

-if the symptoms being treated do not subside or ir redness, irritation, swelling,

pain or other symptoms develop or increase. Some people can develop allergic

reactions to ingredients in this product.

, ask a health professional before use. If pregnant or breast-feeding

- do not put this product into the rectum by using fingers or any mechanical device or applicator
- do not exceed recommended daily dosage unless directed by a doctor

KEEP OUT OF REACH OF CHILDREN

. If swallowed, get medical help or contact a Keep out of reach of children

Poison Control Center right away.

DOSAGE AND ADMINISTRATION

Adults: Directions

-when practical, cleanse the affected area with mild soap and warm water and

rinse thoroughly. Gentlydry by patting or blotting with toilet tissue or a soft

cloth before application of this product.

-apply externally to the affected area up to 4 times daily especially at night r

in the morningor after each bowel movement.

hildren under 12 years of age: consult a doctor.

STORAGE AND HANDLING

store at room temperature 68° - 77° F (20° - 25° C) Other information

aloe barbadensis leaf extract, Inactive ingredients

carboxymethylcellulose sodium, cetyl alcohol, glyceryl monostearate,

methylparaben, paraffin, propylene glycol, propylparaben, stearic acid, tween 80,

water, xanthan gum